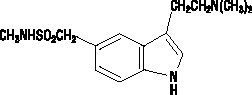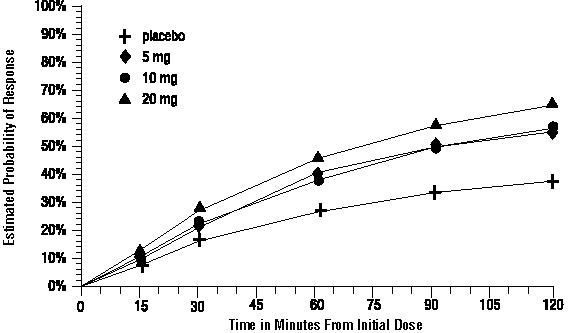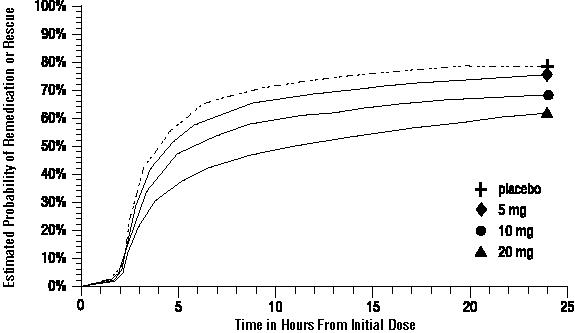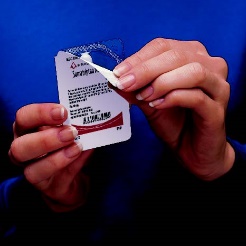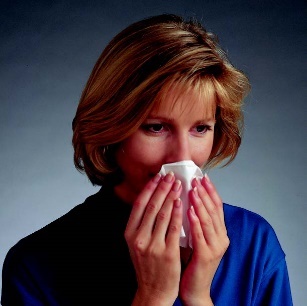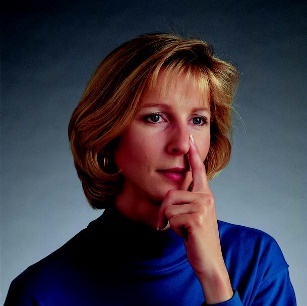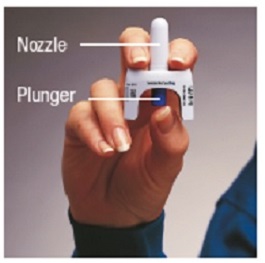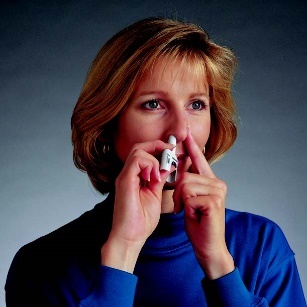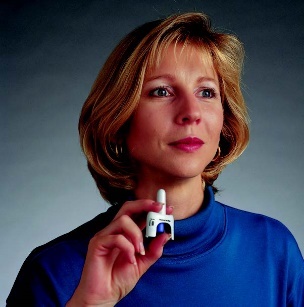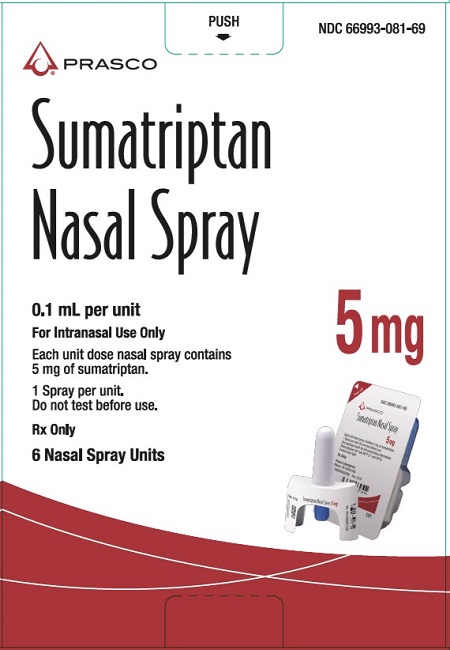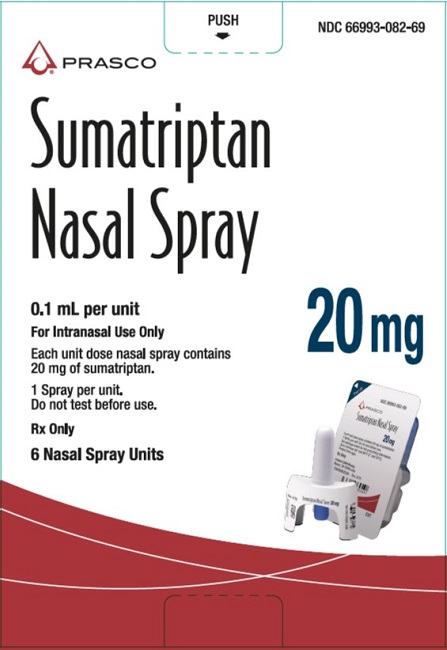 DRUG LABEL: SUMATRIPTAN
NDC: 66993-081 | Form: SPRAY
Manufacturer: Prasco Laboratories
Category: prescription | Type: HUMAN PRESCRIPTION DRUG LABEL
Date: 20260129

ACTIVE INGREDIENTS: SUMATRIPTAN 5 mg/100 uL
INACTIVE INGREDIENTS: MONOBASIC POTASSIUM PHOSPHATE; SODIUM PHOSPHATE, DIBASIC, ANHYDROUS; SULFURIC ACID; SODIUM HYDROXIDE; WATER

HIGHLIGHTS OF PRESCRIBING INFORMATION

These highlights do not include all the information needed to use Sumatriptan Nasal Spray safely and effectively. See full prescribing information for Sumatriptan Nasal Spray.
Sumatriptan nasal spray
Initial U.S. Approval: 1992

1 INDICATIONS AND USAGE

Sumatriptan is a serotonin (5-HT1B/1D) receptor agonist (triptan) indicated for acute treatment of migraine with or without aura in adults. (1)

Limitations of Use:

- Use only if a clear diagnosis of migraine headache has been established. (1)
- Not indicated for the prophylactic therapy of migraine attacks. (1)
- Not indicated for the treatment of cluster headache. (1)

2 DOSAGE AND ADMINISTRATION

- Single dose of 5 mg, 10 mg, or 20 mg of nasal spray. (2)
- A second dose should only be considered if some response to the first dose was observed. Separate doses by at least 2 hours. (2)
- Maximum dose in a 24-hour period: 40 mg. (2)

3 DOSAGE FORMS AND STRENGTHS

Nasal spray: 5 mg and 20 mg (3, 16)

4 CONTRAINDICATIONS

- History of coronary artery disease or coronary artery vasospasm (4)
- Wolff-Parkinson-White syndrome or other cardiac accessory conduction pathway disorders (4)
- History of stroke, transient ischemic attack, or hemiplegic or basilar migraine (4)
- Peripheral vascular disease (4)
- Ischemic bowel disease (4)
- Uncontrolled hypertension (4)
- Recent (within 24 hours) use of another 5-HT1 agonist (e.g., another triptan) or of an ergotamine-containing medication. (4)
- Concurrent or recent (past 2 weeks) use of monoamine oxidase-A inhibitor. (4)
- Hypersensitivity to sumatriptan (angioedema and anaphylaxis seen). (4)
- Severe hepatic impairment (4)

5 WARNINGS AND PRECAUTIONS

- Myocardial ischemia/infarction and Prinzmetal’s angina: Perform cardiac evaluation in patients with multiple cardiovascular risk factors. (5.1)
- Arrhythmias: Discontinue Sumatriptan Nasal Spray if occurs. (5.2)
- Chest/throat/neck/jaw pain, tightness, pressure, or heaviness: Generally not associated with myocardial ischemia; evaluate for coronary artery disease in patients at high risk. (5.3)
- Cerebral hemorrhage, subarachnoid hemorrhage, and stroke: Discontinue Sumatriptan Nasal Spray if occurs. (5.4)
- Gastrointestinal ischemic reactions and peripheral vasospastic reactions: Discontinue Sumatriptan Nasal Spray if occurs. (5.5)
- Medication overuse headache: Detoxification may be necessary. (5.6)
- Serotonin syndrome: Discontinue Sumatriptan Nasal Spray if occurs. (5.7)
- Seizures: Use with caution in patients with epilepsy or a lowered seizure threshold. (5.11)

6 ADVERSE REACTIONS

Most common adverse reactions (≥1% and >placebo) were burning sensation, disorder/discomfort of nasal cavity/sinuses, throat discomfort, nausea and/or vomiting, bad/unusual taste, and dizziness/vertigo. (6.1)

To report SUSPECTED ADVERSE REACTIONS, contact Prasco Laboratories at 1-866-525-0688 or FDA at 1-800-FDA-1088 or www.fda.gov/medwatch.

8 USE IN SPECIFIC POPULATIONS

Pregnancy: Based on animal data, may cause fetal harm. (8.1)

FULL PRESCRIBING INFORMATION

1 INDICATIONS AND USAGE

Sumatriptan Nasal Spray is indicated for the acute treatment of migraine with or without aura in adults.

Limitations of Use:

- Use only if a clear diagnosis of migraine headache has been established. If a patient has no response to the first migraine attack treated with Sumatriptan Nasal Spray, reconsider the diagnosis of migraine before Sumatriptan Nasal Spray is administered to treat any subsequent attacks.
- Sumatriptan is not indicated for the prevention of migraine attacks.
- Safety and effectiveness of Sumatriptan Nasal Spray have not been established for cluster headache.

2 DOSAGE AND ADMINISTRATION

The recommended adult dose of Sumatriptan Nasal Spray for the acute treatment of migraine is 5 mg, 10 mg, or 20 mg. The 20-mg dose may provide a greater effect than the 5-mg and 10-mg doses, but may have a greater risk of adverse reactions [see Clinical Studies (14)].

The 5-mg and 20-mg doses are given as a single spray in 1 nostril. The 10-mg dose may be achieved by the administration of a single 5-mg dose in each nostril.

If the migraine has not resolved by 2 hours after taking Sumatriptan Nasal Spray, or returns after a transient improvement, 1 additional dose may be administered at least 2 hours after the first dose. The maximum daily dose is 40 mg in a 24-hour period.

The safety of treating an average of more than 4 headaches in a 30‑day period has not been established.

3 DOSAGE FORMS AND STRENGTHS

Unit dose nasal spray devices containing 5 mg or 20 mg sumatriptan.

4 CONTRAINDICATIONS

Sumatriptan Nasal Spray is contraindicated in patients with:

- Ischemic coronary artery disease (CAD) (angina pectoris, history of myocardial infarction, or documented silent ischemia) or coronary artery vasospasm, including Prinzmetal’s angina [see Warnings and Precautions (5.1)]
- Wolff-Parkinson-White syndrome or arrhythmias associated with other cardiac accessory conduction pathway disorders [see Warnings and Precautions (5.2)]
- History of stroke, transient ischemic attack (TIA), or history of hemiplegic or basilar migraine because these patients are at a higher risk of stroke [see Warnings and Precautions (5.4)]
- Peripheral vascular disease [see Warnings and Precautions (5.5)]
- Ischemic bowel disease [see Warnings and Precautions (5.5)]
- Uncontrolled hypertension [see Warnings and Precautions (5.8)]
- Recent use (i.e., within 24 hours) of ergotamine-containing medication, ergot-type medication (such as dihydroergotamine or methysergide), or another 5-hydroxytryptamine1 (5-HT1) agonist [see Drug Interactions (7.1, 7.3)]
- Concurrent administration of a monoamine oxidase (MAO)-A inhibitor or recent (within 2 weeks) use of an MAO-A inhibitor [see Drug Interactions (7.2), Clinical Pharmacology (12.3)]
- Hypersensitivity to sumatriptan (angioedema and anaphylaxis seen) [see Warnings and Precautions (5.10)]
- Severe hepatic impairment [see Clinical Pharmacology (12.3)]

5 WARNINGS AND PRECAUTIONS

5.1 Myocardial Ischemia, Myocardial Infarction, and Prinzmetal’s Angina

The use of Sumatriptan Nasal Spray is contraindicated in patients with ischemic or vasospastic CAD. There have been rare reports of serious cardiac adverse reactions, including acute myocardial infarction, occurring within a few hours following administration of Sumatriptan Nasal Spray. Some of these reactions occurred in patients without known CAD. Sumatriptan Nasal Spray may cause coronary artery vasospasm (Prinzmetal’s angina), even in patients without a history of CAD.

Perform a cardiovascular evaluation in triptan-naive patients who have multiple cardiovascular risk factors (e.g., increased age, diabetes, hypertension, smoking, obesity, strong family history of CAD) prior to receiving Sumatriptan Nasal Spray. If there is evidence of CAD or coronary artery vasospasm, Sumatriptan Nasal Spray is contraindicated. For patients with multiple cardiovascular risk factors who have a negative cardiovascular evaluation, consider administering the first dose of Sumatriptan Nasal Spray in a medically supervised setting and performing an electrocardiogram (ECG) immediately following administration of Sumatriptan Nasal Spray. For such patients, consider periodic cardiovascular evaluation in intermittent long-term users of Sumatriptan Nasal Spray.

5.2 Arrhythmias

Life-threatening disturbances of cardiac rhythm, including ventricular tachycardia and ventricular fibrillation leading to death, have been reported within a few hours following the administration of 5-HT1 agonists. Discontinue Sumatriptan Nasal Spray if these disturbances occur. Sumatriptan Nasal Spray is contraindicated in patients with Wolff-Parkinson-White syndrome or arrhythmias associated with other cardiac accessory conduction pathway disorders.

5.3 Chest, Throat, Neck, and/or Jaw Pain/Tightness/Pressure

Sensations of tightness, pain, pressure, and heaviness in the precordium, throat, neck, and jaw may occur after treatment with Sumatriptan Nasal Spray and are usually non-cardiac in origin. However, perform a cardiac evaluation if these patients are at high cardiac risk. The use of Sumatriptan Nasal Spray is contraindicated in patients with CAD and those with Prinzmetal’s variant angina.

5.4 Cerebrovascular Events

Cerebral hemorrhage, subarachnoid hemorrhage, and stroke have occurred in patients treated with 5-HT1 agonists, and some have resulted in fatalities. In a number of cases, it appears possible that the cerebrovascular events were primary, the 5-HT1 agonist having been administered in the incorrect belief that the symptoms experienced were a consequence of migraine when they were not. Also, patients with migraine may be at increased risk of certain cerebrovascular events (e.g., stroke, hemorrhage, TIA). Discontinue Sumatriptan Nasal Spray if a cerebrovascular event occurs.

Before treating headaches in patients not previously diagnosed as migraineurs, and in migraineurs who present with atypical symptoms, exclude other potentially serious neurological conditions. Sumatriptan Nasal Spray is contraindicated in patients with a history of stroke or TIA.

5.5 Other Vasospasm Reactions

Sumatriptan Nasal Spray may cause non-coronary vasospastic reactions, such as peripheral vascular ischemia, gastrointestinal vascular ischemia and infarction (presenting with abdominal pain and bloody diarrhea), splenic infarction, and Raynaud’s syndrome. In patients who experience symptoms or signs suggestive of non-coronary vasospasm reaction following the use of any 5-HT1 agonist, rule out a vasospastic reaction before using additional Sumatriptan Nasal Spray.

Reports of transient and permanent blindness and significant partial vision loss have been reported with the use of 5‑HT1 agonists. Since visual disorders may be part of a migraine attack, a causal relationship between these events and the use of 5-HT1 agonists has not been clearly established.

5.6 Medication Overuse Headache

Overuse of acute migraine drugs (e.g., ergotamine, triptans, opioids, or combination of these drugs for 10 or more days per month) may lead to exacerbation of headache (medication overuse headache). Medication overuse headache may present as migraine-like daily headaches or as a marked increase in frequency of migraine attacks. Detoxification of patients, including withdrawal of the overused drugs, and treatment of withdrawal symptoms (which often includes a transient worsening of headache) may be necessary.

5.7 Serotonin Syndrome

Serotonin syndrome may occur with Sumatriptan Nasal Spray, particularly during coadministration with selective serotonin reuptake inhibitors (SSRIs), serotonin norepinephrine reuptake inhibitors (SNRIs), tricyclic antidepressants (TCAs), and MAO inhibitors [see Drug Interactions (7.4)]. Serotonin syndrome symptoms may include mental status changes (e.g., agitation, hallucinations, coma), autonomic instability (e.g., tachycardia, labile blood pressure, hyperthermia), neuromuscular aberrations (e.g., hyperreflexia, incoordination), and/or gastrointestinal symptoms (e.g., nausea, vomiting, diarrhea). The onset of symptoms usually occurs within minutes to hours of receiving a new or a greater dose of a serotonergic medication. Discontinue Sumatriptan Nasal Spray if serotonin syndrome is suspected.

5.8 Increase in Blood Pressure

Significant elevation in blood pressure, including hypertensive crisis with acute impairment of organ systems, has been reported on rare occasions in patients treated with 5-HT1 agonists, including patients without a history of hypertension. Monitor blood pressure in patients treated with sumatriptan. Sumatriptan Nasal Spray is contraindicated in patients with uncontrolled hypertension.

5.9 Local Irritation

Local irritative symptoms such as burning, numbness, paresthesia, discharge, and pain or soreness were reported in approximately 5% of patients in controlled clinical trials and were noted to be severe in about 1%. The symptoms were transient and generally resolved in less than 2 hours. Limited examinations of the nose and throat did not reveal any clinically noticeable injury in these patients. The consequences of extended and repeated use of Sumatriptan Nasal Spray on the nasal and/or respiratory mucosa have not been systematically evaluated in patients.

5.10 Anaphylactic/Anaphylactoid Reactions

Anaphylactic/anaphylactoid reactions have occurred in patients receiving sumatriptan. Such reactions can be life-threatening or fatal. In general, anaphylactic reactions to drugs are more likely to occur in individuals with a history of sensitivity to multiple allergens. Sumatriptan Nasal Spray is contraindicated in patients with a history of hypersensitivity reaction to sumatriptan.

5.11 Seizures

Seizures have been reported following administration of sumatriptan. Some have occurred in patients with either a history of seizures or concurrent conditions predisposing to seizures. There are also reports in patients where no such predisposing factors are apparent. Sumatriptan Nasal Spray should be used with caution in patients with a history of epilepsy or conditions associated with a lowered seizure threshold.

6 ADVERSE REACTIONS

The following adverse reactions are discussed in more detail in other sections of the prescribing information:

- Myocardial ischemia, myocardial infarction, and Prinzmetal’s angina [see Warnings and Precautions (5.1)]
- Arrhythmias [see Warnings and Precautions (5.2)]
- Chest, throat, neck, and/or jaw pain/tightness/pressure [see Warnings and Precautions (5.3)]
- Cerebrovascular events [see Warnings and Precautions (5.4)]
- Other vasospasm reactions [see Warnings and Precautions (5.5)]
- Medication overuse headache [see Warnings and Precautions (5.6)]
- Serotonin syndrome [see Warnings and Precautions (5.7)]
- Increase in blood pressure [see Warnings and Precautions (5.8)]
- Local irritation [see Warnings and Precautions (5.9)]
- Hypersensitivity reactions [see Contraindications (4), Warnings and Precautions (5.10)]
- Seizures [see Warnings and Precautions (5.11)]

6.1 Clinical Trials Experience

Because clinical trials are conducted under widely varying conditions, adverse reaction rates observed in the clinical trials of a drug cannot be directly compared with rates in the clinical trials of another drug and may not reflect the rates observed in practice.

Table 1 lists adverse reactions that occurred in worldwide placebo-controlled clinical trials in 3,419 patients with migraine. Only treatment-emergent adverse reactions that occurred at a frequency of 1% or more in the group treated with Sumatriptan Nasal Spray 20 mg and that occurred at a frequency greater than the placebo group are included in Table 1.

Table 1. Adverse Reactions Reported by at Least 1% of Patients and at a Greater Frequency than Placebo in Controlled Migraine Clinical Trials
Adverse Reaction | Percent of Patients Reporting
Adverse Reaction | Sumatriptan; Nasal Spray; 5 mg; (n = 496) | Sumatriptan; Nasal Spray; 10 mg; (n = 1,007) | Sumatriptan; Nasal Spray; 20 mg; (n = 1,212) | Placebo; (n = 704)
Atypical sensations
Burning sensation | 0.4 | 0.6 | 1.4 | 0.1
Ear, nose, and throat
Disorder/discomfort of nasal cavity/sinuses | 2.8 | 2.5 | 3.8 | 2.4
Throat discomfort | 0.8 | 1.8 | 2.4 | 0.9
Gastrointestinal
Nausea and/or vomiting | 12.2 | 11.0 | 13.5 | 11.3
Neurological
Bad/unusual taste | 13.5 | 19.3 | 24.5 | 1.7
Dizziness/vertigo | 1.0 | 1.7 | 1.4 | 0.9

The incidence of adverse reactions in controlled clinical trials was not affected by gender, weight, or age of the patients; use of prophylactic medications; or presence of aura. There were insufficient data to assess the impact of race on the incidence of adverse reactions.

6.2 Postmarketing Experience

The following adverse reactions have been identified during postapproval use of sumatriptan tablets, sumatriptan nasal spray, and sumatriptan injection. Because these reactions are reported voluntarily from a population of uncertain size, it is not always possible to reliably estimate their frequency or establish a causal relationship to drug exposure. These reactions have been chosen for inclusion due to either their seriousness, frequency of reporting, or causal connection to sumatriptan or a combination of these factors.

Cardiovascular

Hypotension, palpitations.

Neurological

Dystonia, tremor.

Reproductive System and Breast Disorders

Breast pain [see Use in Specific Populations (8.2)].

7 DRUG INTERACTIONS

7.1 Ergot-Containing Drugs

Ergot-containing drugs have been reported to cause prolonged vasospastic reactions. Because these effects may be additive, use of ergotamine-containing or ergot-type medications (like dihydroergotamine or methysergide) and Sumatriptan Nasal Spray within 24 hours of each other is contraindicated.

7.2 Monoamine Oxidase-A Inhibitors

MAO-A inhibitors increase systemic exposure by up to 7-fold. Therefore, the use of Sumatriptan Nasal Spray in patients receiving MAO-A inhibitors is contraindicated [see Clinical Pharmacology (12.3)].

7.3 Other 5-HT1 Agonists

Because their vasospastic effects may be additive, coadministration of Sumatriptan Nasal Spray and other 5-HT1 agonists (e.g., triptans) within 24 hours of each other is contraindicated.

7.4 Selective Serotonin Reuptake Inhibitors/Serotonin Norepinephrine Reuptake Inhibitors and Serotonin Syndrome

Cases of serotonin syndrome have been reported during coadministration of triptans and SSRIs, SNRIs, TCAs, and MAO inhibitors [see Warnings and Precautions (5.7)].

8 USE IN SPECIFIC POPULATIONS

8.1 Pregnancy

Risk Summary

Data from a prospective pregnancy exposure registry and epidemiological studies of pregnant women have not detected an increased frequency of birth defects or a consistent pattern of birth defects among women exposed to sumatriptan compared with the general population (see Data). In developmental toxicity studies in rats and rabbits, oral administration of sumatriptan to pregnant animals was associated with embryolethality, fetal abnormalities, and pup mortality. When administered by the intravenous route to pregnant rabbits, sumatriptan was embryolethal (see Data).

In the U.S. general population, the estimated background risk of major birth defects and of miscarriage in clinically recognized pregnancies is 2% to 4% and 15% to 20%, respectively. The reported rate of major birth defects among deliveries to women with migraine ranged from 2.2% to 2.9% and the reported rate of miscarriage was 17%, which were similar to rates reported in women without migraine.

Clinical Considerations

Disease-Associated Maternal and/or Embryo/Fetal Risk: Several studies have suggested that women with migraine may be at increased risk of preeclampsia during pregnancy.

Data

Human Data: The Sumatriptan/Naratriptan/TREXIMET (sumatriptan and naproxen sodium) Pregnancy Registry, a population-based international prospective study, collected data for sumatriptan from January 1996 to September 2012. The Registry documented outcomes of 626 infants and fetuses exposed to sumatriptan during pregnancy (528 with earliest exposure during the first trimester, 78 during the second trimester, 16 during the third trimester, and 4 unknown). The occurrence of major birth defects (excluding fetal deaths and induced abortions without reported defects and all spontaneous pregnancy losses) during first-trimester exposure to sumatriptan was 4.2% (20/478 [95% CI: 2.6% to 6.5%]) and during any trimester of exposure was 4.2% (24/576 [95% CI: 2.7% to 6.2%]). The sample size in this study had 80% power to detect at least a 1.73- to 1.91-fold increase in the rate of major malformations. The number of exposed pregnancy outcomes accumulated during the registry was insufficient to support definitive conclusions about overall malformation risk or for making comparisons of the frequencies of specific birth defects. Of the 20 infants with reported birth defects after exposure to sumatriptan in the first trimester, 4 infants had ventricular septal defects, including one infant who was exposed to both sumatriptan and naratriptan, and 3 infants had pyloric stenosis. No other birth defect was reported for more than 2 infants in this group.

In a study using data from the Swedish Medical Birth Register, live births to women who reported using triptans or ergots during pregnancy were compared with those of women who did not. Of the 2,257 births with first-trimester exposure to sumatriptan, 107 infants were born with malformations (relative risk 0.99 [95% CI: 0.91 to 1.21]). A study using linked data from the Medical Birth Registry of Norway to the Norwegian Prescription Database compared pregnancy outcomes in women who redeemed prescriptions for triptans during pregnancy, as well as a migraine disease comparison group who redeemed prescriptions for sumatriptan before pregnancy only, compared with a population control group. Of the 415 women who redeemed prescriptions for sumatriptan during the first trimester, 15 had infants with major congenital malformations (OR 1.16 [95% CI: 0.69 to 1.94]) while for the 364 women who redeemed prescriptions for sumatriptan before, but not during, pregnancy, 20 had infants with major congenital malformations (OR 1.83 [95% CI: 1.17 to 2.88]), each compared with the population comparison group. Additional smaller observational studies evaluating use of sumatriptan during pregnancy have not suggested an increased risk of teratogenicity.

Animal Data: Oral administration of sumatriptan to pregnant rats during the period of organogenesis resulted in an increased incidence of fetal blood vessel (cervicothoracic and umbilical) abnormalities. The highest no-effect dose for embryofetal developmental toxicity in rats was 60 mg/kg/day. Oral administration of sumatriptan to pregnant rabbits during the period of organogenesis resulted in increased incidences of embryolethality and fetal cervicothoracic vascular and skeletal abnormalities. Intravenous administration of sumatriptan to pregnant rabbits during the period of organogenesis resulted in an increased incidence of embryolethality. The highest oral and intravenous no-effect doses for developmental toxicity in rabbits were 15 and 0.75 mg/kg/day, respectively.

Oral administration of sumatriptan to rats prior to and throughout gestation resulted in embryofetal toxicity (decreased body weight, decreased ossification, increased incidence of skeletal abnormalities). The highest no-effect dose was 50 mg/kg/day. In offspring of pregnant rats treated orally with sumatriptan during organogenesis, there was a decrease in pup survival. The highest no-effect dose for this effect was 60 mg/kg/day. Oral treatment of pregnant rats with sumatriptan during the latter part of gestation and throughout lactation resulted in a decrease in pup survival. The highest no-effect dose for this finding was 100 mg/kg/day.

8.2 Lactation

Risk Summary

Sumatriptan is excreted in human milk following subcutaneous administration. There is no information regarding sumatriptan concentrations in milk from lactating women following administration of Sumatriptan Nasal Spray. There are no data on the effects of sumatriptan on the breastfed infant or the effects of sumatriptan on milk production. Use of sumatriptan may be associated with transient breast pain [see Adverse Reactions (6.2)].

The developmental and health benefits of breastfeeding should be considered along with the mother’s clinical need for Sumatriptan Nasal Spray and any potential adverse effects on the breastfed infant from sumatriptan or from the underlying maternal condition.

Clinical Considerations

Infant exposure to sumatriptan can be minimized by avoiding breastfeeding for 12 hours after treatment with Sumatriptan Nasal Spray.

8.4 Pediatric Use

Safety and effectiveness in pediatric patients have not been established. Sumatriptan Nasal Spray is not recommended for use in patients younger than 18 years of age.

Two controlled clinical trials evaluated Sumatriptan Nasal Spray (5 to 20 mg) in 1,248 adolescent migraineurs aged 12 to 17 years who treated a single attack. The trials did not establish the efficacy of Sumatriptan Nasal Spray compared with placebo in the treatment of migraine in adolescents. Adverse reactions observed in these clinical trials were similar in nature to those reported in clinical trials in adults.

Five controlled clinical trials (2 single-attack trials, 3 multiple-attack trials) evaluating oral sumatriptan (25 to 100 mg) in pediatric patients aged 12 to 17 years enrolled a total of 701 adolescent migraineurs. These trials did not establish the efficacy of oral sumatriptan compared with placebo in the treatment of migraine in adolescents. Adverse reactions observed in these clinical trials were similar in nature to those reported in clinical trials in adults. The frequency of all adverse reactions in these patients appeared to be both dose- and age-dependent, with younger patients reporting reactions more commonly than older adolescents.

Postmarketing experience documents that serious adverse reactions have occurred in the pediatric population after use of subcutaneous, oral, and/or intranasal sumatriptan. These reports include reactions similar in nature to those reported rarely in adults, including stroke, visual loss, and death. A myocardial infarction has been reported in a 14‑year‑old male following the use of oral sumatriptan; clinical signs occurred within 1 day of drug administration. Clinical data to determine the frequency of serious adverse reactions in pediatric patients who might receive subcutaneous, oral, or intranasal sumatriptan are not presently available.

8.5 Geriatric Use

Clinical trials of Sumatriptan Nasal Spray did not include sufficient numbers of patients aged 65 years and older to determine whether they respond differently from younger patients. Other reported clinical experience has not identified differences in responses between the elderly and younger patients. In general, dose selection for an elderly patient should be cautious, usually starting at the low end of the dosing range, reflecting the greater frequency of decreased hepatic, renal, or cardiac function and of concomitant disease or other drug therapy.

A cardiovascular evaluation is recommended for geriatric patients who have other cardiovascular risk factors (e.g., diabetes, hypertension, smoking, obesity, strong family history of CAD) prior to receiving Sumatriptan Nasal Spray [see Warnings and Precautions (5.1)].

10 OVERDOSAGE

In clinical trials, the highest single doses of Sumatriptan Nasal Spray administered without significant reactions were 40 mg to 12 volunteers and 40 mg to 85 subjects with migraine, which is twice the highest single recommended dose. In addition, 12 volunteers were administered a total daily dose of 60 mg (20 mg 3 times daily) for 3.5 days without significant adverse reactions.

Overdose in animals has been fatal and has been heralded by convulsions, tremor, paralysis, inactivity, ptosis, erythema of the extremities, abnormal respiration, cyanosis, ataxia, mydriasis, salivation, and lacrimation.

The elimination half‑life of sumatriptan is approximately 2 hours [see Clinical Pharmacology (12.3)], and therefore monitoring of patients after overdose with Sumatriptan Nasal Spray should continue for at least 10 hours or while symptoms or signs persist.

It is unknown what effect hemodialysis or peritoneal dialysis has on the serum concentrations of sumatriptan.

11 DESCRIPTION

Sumatriptan Nasal Spray contains sumatriptan, a selective 5-HT1B/1D receptor agonist. Sumatriptan is chemically designated as 3-[2-(dimethylamino)ethyl]-N-methyl-indole-5-methanesulfonamide, and it has the following structure:

The empirical formula is C14H21N3O2S, representing a molecular weight of 295.4. Sumatriptan is a white to off-white powder that is readily soluble in water and in saline.

Each Sumatriptan Nasal Spray contains 5 or 20 mg of sumatriptan in a 100-mcL unit dose aqueous buffered solution containing monobasic potassium phosphate NF, anhydrous dibasic sodium phosphate USP, sulfuric acid NF, sodium hydroxide NF, and purified water USP. The pH of the solution is approximately 5.5. The osmolality of the solution is 372 or 742 mOsmol for the 5- and 20-mg Sumatriptan Nasal Spray, respectively.

12 CLINICAL PHARMACOLOGY

12.1 Mechanism of Action

Sumatriptan binds with high affinity to human cloned 5-HT1B/1D receptors. Sumatriptan presumably exerts its therapeutic effects in the treatment of migraine headache through agonist effects at the 5‑HT1B/1D receptors on intracranial blood vessels and sensory nerves of the trigeminal system, which result in cranial vessel constriction and inhibition of pro-inflammatory neuropeptide release.

12.2 Pharmacodynamics

Blood Pressure

Significant elevation in blood pressure, including hypertensive crisis, has been reported in patients with and without a history of hypertension [see Warnings and Precautions (5.8)].

Peripheral (Small) Arteries

In healthy volunteers (N = 18), a trial evaluating the effects of sumatriptan on peripheral (small vessel) arterial reactivity failed to detect a clinically significant increase in peripheral resistance.

Heart Rate

Transient increases in blood pressure observed in some patients in clinical trials carried out during sumatriptan’s development as a treatment for migraine were not accompanied by any clinically significant changes in heart rate.

12.3 Pharmacokinetics

Absorption

In a trial of 20 female volunteers, the mean maximum concentration following a 5- and 20-mg intranasal dose was 5 and 16 ng/mL, respectively. The mean Cmax following a 6‑mg subcutaneous injection is 71 ng/mL (range: 49 to 110 ng/mL). The mean Cmax is 18 ng/mL (range: 7 to 47 ng/mL) following oral dosing with 25 mg and 51 ng/mL (range: 28 to 100 ng/mL) following oral dosing with 100 mg of sumatriptan. In a trial of 24 male volunteers, the bioavailability relative to subcutaneous injection was low, approximately 17%, primarily due to presystemic metabolism and partly due to incomplete absorption.

Clinical and pharmacokinetic data indicate that administration of two 5-mg doses, 1 dose in each nostril, is equivalent to administration of a single 10-mg dose in 1 nostril.

Distribution

Protein binding, determined by equilibrium dialysis over the concentration range of 10 to 1,000 ng/mL, is low, approximately 14% to 21%. The effect of sumatriptan on the protein binding of other drugs has not been evaluated. The apparent volume of distribution is 2.7 L/kg.

Metabolism

In vitro studies with human microsomes suggest that sumatriptan is metabolized by MAO, predominantly the A isoenzyme. Most of a radiolabeled dose of sumatriptan excreted in the urine is the major metabolite indole acetic acid (IAA) or the IAA glucuronide, both of which are inactive.

Elimination

The elimination half-life of sumatriptan administered as a nasal spray is approximately 2 hours, similar to the half-life seen after subcutaneous injection. Only 3% of the dose is excreted in the urine as unchanged sumatriptan; 42% of the dose is excreted as the major metabolite, the indole acetic acid analogue of sumatriptan. The total plasma clearance is approximately 1,200 mL/min.

Specific Populations

Age: The pharmacokinetics of sumatriptan in the elderly (mean age: 72 years, 2 males and 4 females) and in subjects with migraine (mean age: 38 years, 25 males and 155 females) were similar to that in healthy male subjects (mean age: 30 years). Intranasal sumatriptan has not been evaluated for age differences.

Patients with Renal Impairment: The effect of renal impairment on the pharmacokinetics of sumatriptan has not been examined.

Patients with Hepatic Impairment: The effect of mild to moderate hepatic disease on the pharmacokinetics of the intranasal formulation of sumatriptan has not been evaluated. Sumatriptan bioavailability following intranasal administration is 17%, similar to that after oral administration (15%). Following oral administration, an approximately 70% increase in Cmax and AUC was observed in one small trial of patients with moderate liver impairment (n = 8) matched for sex, age, and weight with healthy subjects (n = 8). Similar changes can be expected following intranasal administration.

The pharmacokinetics of sumatriptan in patients with severe hepatic impairment has not been studied. The use of Sumatriptan Nasal Spray in patients with severe hepatic impairment is contraindicated [see Contraindications (4)].

Racial Groups: The systemic clearance and Cmax of subcutaneous sumatriptan were similar in black (n = 34) and Caucasian (n = 38) healthy male subjects. Intranasal sumatriptan has not been evaluated for race differences.

Drug Interaction Studies

Monoamine Oxidase-A Inhibitors: Treatment with MAO-A inhibitors generally leads to an increase of sumatriptan plasma levels [see Contraindications (4), Drug Interactions (7.2)]. MAO inhibitors interaction studies have not been performed with intranasal sumatriptan.

Due to gut and hepatic metabolic first-pass effects, the increase of systemic exposure after coadministration of an MAO-A inhibitor with oral sumatriptan is greater than after coadministration of the MAO inhibitors with subcutaneous sumatriptan. The effects of an MAO inhibitor on systemic exposure after intranasal sumatriptan would be expected to be greater than the effect after subcutaneous sumatriptan but smaller than the effect after oral sumatriptan because only swallowed drug would be subject to first-pass effects.

In a trial of 14 healthy females, pretreatment with an MAO-A inhibitor decreased the clearance of subcutaneous sumatriptan, resulting in a 2-fold increase in the area under the sumatriptan plasma concentration-time curve (AUC), corresponding to a 40% increase in elimination half‑life.

A small trial evaluating the effect of pretreatment with an MAO-A inhibitor on the bioavailability from a 25-mg oral sumatriptan tablet resulted in an approximately 7-fold increase in systemic exposure.

Xylometazoline: An in vivo drug interaction trial indicated that 3 drops of xylometazoline (0.1% w/v), a decongestant, administered 15 minutes prior to a 20-mg nasal dose of sumatriptan did not alter the pharmacokinetics of sumatriptan.

13 NONCLINICAL TOXICOLOGY

13.1 Carcinogenesis, Mutagenesis, Impairment of Fertility

Carcinogenesis

In carcinogenicity studies in mouse and rat in which sumatriptan was administered orally for 78 and 104 weeks, respectively, there was no evidence in either species of an increase in tumors related to sumatriptan administration.

Carcinogenicity studies of sumatriptan using the nasal route have not been conducted.

Mutagenesis

Sumatriptan was negative in in vitro (bacterial reverse mutation [Ames], gene cell mutation in Chinese hamster V79/HGPRT, chromosomal aberration in human lymphocytes) and in vivo (rat micronucleus) assays.

Impairment of Fertility

When sumatriptan (5, 50, or 500 mg/kg/day) was administered orally to male and female rats prior to and throughout the mating period, there was a treatment-related decrease in fertility secondary to a decrease in mating in animals treated with doses greater than 5 mg/kg/day. It is not clear whether this finding was due to an effect on males or females or both.

When sumatriptan was administered by subcutaneous injection to male and female rats prior to and throughout the mating period, there was no evidence of impaired fertility at doses up to 60 mg/kg/day.

Fertility studies of sumatriptan using the intranasal route have not been conducted.

13.2 Animal Toxicology and/or Pharmacology

Corneal Opacities

Dogs receiving oral sumatriptan developed corneal opacities and defects in the corneal epithelium. Corneal opacities were seen at the lowest dose tested, 2 mg/kg/day, and were present after 1 month of treatment. Defects in the corneal epithelium were noted in a 60‑week study. Earlier examinations for these toxicities were not conducted and no-effect doses were not established.

14 CLINICAL STUDIES

The efficacy of Sumatriptan Nasal Spray in the acute treatment of migraine headaches was demonstrated in 8 randomized, double-blind, placebo-controlled trials, of which 5 used the recommended dosing regimen and used the marketed formulation. Patients enrolled in these 5 trials were predominately female (86%) and Caucasian (95%), with a mean age of 41 years (range: 18 to 65 years). Patients were instructed to treat a moderate to severe headache. Headache response, defined as a reduction in headache severity from moderate or severe pain to mild or no pain, was assessed up to 2 hours after dosing. Associated symptoms such as nausea, photophobia, and phonophobia were also assessed. Maintenance of response was assessed for up to 24 hours postdose. A second dose of Sumatriptan Nasal Spray or other medication was allowed 2 to 24 hours after the initial treatment for recurrent headache. The frequency and time to use of these additional treatments were also determined. In all trials, doses of 10 and 20 mg were compared with placebo in the treatment of 1 to 3 migraine attacks. Patients received doses as a single spray into 1 nostril. In 2 trials, a 5-mg dose was also evaluated.

In all 5 trials utilizing the market formulation and recommended dosage regimen, the percentage of patients achieving headache response 2 hours after treatment was significantly greater among patients receiving Sumatriptan Nasal Spray at all doses (with one exception) compared with those who received placebo. In 4 of the 5 trials, there was a statistically significant greater percentage of patients with headache response at 2 hours in the 20-mg group when compared with the lower-dose groups (5 and 10 mg). There were no statistically significant differences between the 5- and 10-mg dose groups in any trial. The results from the 5 controlled clinical trials are summarized in Table 2. Note that, in general, comparisons of results obtained in trials conducted under different conditions by different investigators with different samples of patients are ordinarily unreliable for purposes of quantitative comparison.

Table 2. Percentage of Patients with Headache Response (No or Mild Pain) 2 Hours following Treatment
 | Sumatriptan; Nasal Spray; 5 mg | Sumatriptan; Nasal Spray; 10 mg | Sumatriptan; Nasal Spray; 20 mg | Placebo
Trial 1 | 49%a | 46%a | 64%a,b,c | 25%
 | (n = 121) | (n = 112) | (n = 118) | (n = 63)
Trial 2 | Not applicable | 44%a | 55%a,b | 25%
 |  | (n = 273) | (n = 277) | (n = 138)
Trial 3 | Not applicable | 54%a | 63%a | 35%
 |  | (n = 106) | (n = 202) | (n = 100)
Trial 4 | Not applicable | 43% | 62%a,b | 29%
 |  | (n = 106) | (n = 215) | (n = 112)
Trial 5d | 45%a | 53%a | 60%a,c | 36%
 | (n = 296) | (n = 291) | (n = 286) | (n = 198)
a P<0.05 in comparison with placebo.
b P<0.05 in comparison with 10 mg.
c P<0.05 in comparison with 5 mg.
d Data are for attack 1 only of multi-attack trial for comparison.

The estimated probability of achieving an initial headache response over the 2 hours following treatment is depicted in Figure 1.

Figure 1. Estimated Probability of Achieving Initial Headache Response within 120 Minutesa

a The figure shows the probability over time of obtaining headache response (no or mild pain) following treatment with intranasal sumatriptan. The averages displayed are based on pooled data from the 5 clinical controlled trials providing evidence of efficacy. Kaplan-Meier plot with patients not achieving response within 120 minutes censored to 120 minutes.

For patients with migraine-associated nausea, photophobia, and phonophobia at baseline, there was a lower incidence of these symptoms at 2 hours following administration of Sumatriptan Nasal Spray compared with placebo.

Two to 24 hours following the initial dose of study treatment, patients were allowed to use additional treatment for pain relief in the form of a second dose of study treatment or other medication. The estimated probability of patients taking a second dose or other medication for migraine over the 24 hours following the initial dose of study treatment is summarized in Figure 2.

Figure 2. The Estimated Probability of Patients Taking a Second Dose or Other Medication for Migraine over the 24 Hours following the Initial Dose of Study Treatmenta

a Kaplan-Meier plot based on data obtained in the 3 clinical controlled trials providing evidence of efficacy with patients not using additional treatments censored to 24 hours. Plot also includes patients who had no response to the initial dose. No remedication was allowed within 2 hours postdose.

There is evidence that doses above 20 mg do not provide a greater effect than 20 mg. There was no evidence to suggest that treatment with sumatriptan was associated with an increase in the severity of recurrent headaches. The efficacy of Sumatriptan Nasal Spray was unaffected by presence of aura; duration of headache prior to treatment; gender, age, or weight of the subject; or concomitant use of common migraine prophylactic drugs (e.g., beta-blockers, calcium channel blockers, tricyclic antidepressants). There were insufficient data to assess the impact of race on efficacy.

16 HOW SUPPLIED/STORAGE AND HANDLING

Sumatriptan Nasal Spray 5 mg (NDC 66993-081-69) and 20 mg (NDC 66993-082-69) are each supplied in boxes of 6 nasal spray devices. Each unit dose spray supplies 5 mg and 20 mg, respectively, of sumatriptan.

Store between 2°C and 30°C (36°F and 86°F). Protect from light.

17 PATIENT COUNSELING INFORMATION

Advise the patient to read the FDA-approved patient labeling (Patient Information and Instructions for Use).

Risk of Myocardial Ischemia and/or Infarction, Prinzmetal’s Angina, Other Vasospasm-Related Events, Arrhythmias, and Cerebrovascular Events

Inform patients that Sumatriptan Nasal Spray may cause serious cardiovascular side effects such as myocardial infarction or stroke. Although serious cardiovascular events can occur without warning symptoms, patients should be alert for the signs and symptoms of chest pain, shortness of breath, irregular heartbeat, significant rise in blood pressure, weakness, and slurring of speech and should ask for medical advice if any indicative sign or symptoms are observed. Apprise patients of the importance of this follow-up [see Warnings and Precautions (5.1, 5.2, 5.4, 5.5, 5.8)].

Anaphylactic/Anaphylactoid Reactions

Inform patients that anaphylactic/anaphylactoid reactions have occurred in patients receiving Sumatriptan Nasal Spray. Such reactions can be life-threatening or fatal. In general, anaphylactic reactions to drugs are more likely to occur in individuals with a history of sensitivity to multiple allergens [see Contraindications (4), Warnings and Precautions (5.10)].

Concomitant Use with Other Triptans or Ergot Medications

Inform patients that use of Sumatriptan Nasal Spray within 24 hours of another triptan or an ergot-type medication (including dihydroergotamine or methysergide) is contraindicated [see Contraindications (4), Drug Interactions (7.1, 7.3)].

Serotonin Syndrome

Caution patients about the risk of serotonin syndrome with the use of Sumatriptan Nasal Spray or other triptans, particularly during combined use with SSRIs, SNRIs, TCAs, and MAO inhibitors [see Warnings and Precautions (5.7), Drug Interactions (7.4)].

Medication Overuse Headache

Inform patients that use of acute migraine drugs for 10 or more days per month may lead to an exacerbation of headache and encourage patients to record headache frequency and drug use (e.g., by keeping a headache diary) [see Warnings and Precautions (5.6)].

Pregnancy

Advise patients to notify their healthcare provider if they become pregnant during treatment or plan to become pregnant [see Use in Specific Populations (8.1)].

Lactation

Advise breastfeeding women that they may develop transient breast pain when taking sumatriptan. Advise breastfeeding women that avoiding breastfeeding for 12 hours after treatment with sumatriptan can minimize their infant’s exposure to sumatriptan [see Use in Specific Populations (8.2)].

Ability to Perform Complex Tasks

Treatment with Sumatriptan Nasal Spray may cause somnolence and dizziness; instruct patients to evaluate their ability to perform complex tasks after administration of Sumatriptan Nasal Spray.

Local Irritation

Inform patients that they may experience local irritation of their nose and throat. The symptoms will generally resolve in less than 2 hours.

How to Use Sumatriptan Nasal Spray

Provide patients instruction on the proper use of Sumatriptan Nasal Spray. Caution patients to avoid spraying the contents of the device in their eyes.
Manufactured by:

GlaxoSmithKline

Durham, NC 27701

Manufactured for:

Prasco Laboratories

Mason, OH 45040 USA

SNS-PS:3PI

PATIENT INFORMATION

Sumatriptan Nasal Spray

(soo” ma trip’ tan)

What is the most important information I should know about Sumatriptan Nasal Spray?

Sumatriptan Nasal Spray can cause serious side effects, including:

Heart attack and other heart problems. Heart problems may lead to death.

Stop taking Sumatriptan Nasal Spray and get emergency medical help right away if you have any of the following symptoms of a heart attack:

- discomfort in the center of your chest that lasts for more than a few minutes, or that goes away and comes back
- severe tightness, pain, pressure, or heaviness in your chest, throat, neck, or jaw
- pain or discomfort in your arms, back, neck, jaw, or stomach
- shortness of breath with or without chest discomfort
- breaking out in a cold sweat
- nausea or vomiting
- feeling lightheaded

Sumatriptan Nasal Spray is not for people with risk factors for heart disease unless a heart exam is done and shows no problem. You have a higher risk for heart disease if you:

- have high blood pressure
- have high cholesterol levels
- smoke
- are overweight
- have diabetes
- have a family history of heart disease

What is Sumatriptan Nasal Spray?

Sumatriptan Nasal Spray is a prescription medicine used to treat acute migraine headaches with or without aura in adults.

Sumatriptan Nasal Spray is not used to treat other types of headaches such as hemiplegic (that make you unable to move on one side of your body) or basilar (rare form of migraine with aura) migraines.

Sumatriptan Nasal Spray is not used to prevent or decrease the number of migraine headaches you have.

It is not known if Sumatriptan Nasal Spray is safe and effective to treat cluster headaches.

It is not known if Sumatriptan Nasal Spray is safe and effective in children under 18 years of age.

Do not use Sumatriptan Nasal Spray if you have:

- heart problems or a history of heart problems
- narrowing of blood vessels to your legs, arms, stomach, or kidneys (peripheral vascular disease)
- uncontrolled high blood pressure
- severe liver problems
- hemiplegic migraines or basilar migraines. If you are not sure if you have these types of migraines, ask your healthcare provider.
- had a stroke, transient ischemic attacks (TIAs), or problems with your blood circulation
- taken any of the following medicines in the last 24 hours:

- almotriptan (AXERT)
- frovatriptan (FROVA)
- rizatriptan (MAXALT, MAXALT-MLT)
- ergotamines (CAFERGOT, ERGOMAR, MIGERGOT)
- dihydroergotamine (D.H.E. 45, MIGRANAL)

- eletriptan (RELPAX)
- naratriptan (AMERGE)
- sumatriptan and naproxen (TREXIMET)
- sumatriptan (IMITREX, ALSUMA, SUMAVEL, DosePro, ZECUITY)

Ask your healthcare provider if you are not sure if your medicine is listed above.
2. an allergy to sumatriptan or any of the ingredients in Sumatriptan Nasal Spray. See the end of this leaflet for a complete list of ingredients in Sumatriptan Nasal Spray.

Before you use Sumatriptan Nasal Spray, tell your healthcare provider about all of your medical conditions, including if you:

- have high blood pressure.
- have high cholesterol.
- have diabetes.
- smoke.
- are overweight.
- have heart problems or family history of heart problems or stroke.
- have kidney problems.
- have liver problems.
- have had epilepsy or seizures.
- are not using effective birth control.
- are pregnant or plan to become pregnant. It is not known if Sumatriptan Nasal Spray can harm your unborn baby.
- are breastfeeding or plan to breastfeed. Sumatriptan Nasal Spray passes into your breast milk. It is not known if this can harm your baby. Talk with your healthcare provider about the best way to feed your baby if you use Sumatriptan Nasal Spray.

Tell your healthcare provider about all the medicines you take, including prescription and over-the-counter medicines, vitamins, and herbal supplements.

Sumatriptan Nasal Spray and certain other medicines can affect each other, causing serious side effects.

Especially tell your healthcare provider if you take antidepressant medicines called:

- selective serotonin reuptake inhibitors (SSRIs)
- serotonin norepinephrine reuptake inhibitors (SNRIs)
- tricyclic antidepressants (TCAs)
- monoamine oxidase inhibitors (MAOIs)

Ask your healthcare provider or pharmacist for a list of these medicines if you are not sure.

Know the medicines you take. Keep a list of them to show your healthcare provider or pharmacist when you get a new medicine.

How should I use Sumatriptan Nasal Spray?

- Certain people should use their first dose of Sumatriptan Nasal Spray in their healthcare provider’s office or in another medical setting. Ask your healthcare provider if you should use your first dose in a medical setting.
- Use Sumatriptan Nasal Spray exactly as your healthcare provider tells you to use it.
- Your healthcare provider may change your dose. Do not change your dose without first talking with your healthcare provider.
- If you do not get any relief after your first nasal spray, do not use a second nasal spray without first talking with your healthcare provider.
- If your headache comes back after the first nasal spray or you only get some relief from your headache, you can use a second nasal spray 2 hours after the first nasal spray.
- Do not use more than 40 mg of Sumatriptan Nasal Spray in a 24‑hour period.
- It is not known how using Sumatriptan Nasal Spray for a long time affects the nose and throat.
- If you use too much Sumatriptan Nasal Spray, call your healthcare provider or go to the nearest hospital emergency room right away.
- You should write down when you have headaches and when you use Sumatriptan Nasal Spray so you can talk with your healthcare provider about how Sumatriptan Nasal Spray is working for you.

What should I avoid while using Sumatriptan Nasal Spray?

Sumatriptan Nasal Spray can cause dizziness, weakness, or drowsiness. If you have these symptoms, do not drive a car, use machinery, or do anything where you need to be alert.

What are the possible side effects of Sumatriptan Nasal Spray?

Sumatriptan Nasal Spray may cause serious side effects. See “What is the most important information I should know about Sumatriptan Nasal Spray?”

These serious side effects include:

- changes in color or sensation in your fingers and toes (Raynaud’s syndrome)
- stomach and intestinal problems (gastrointestinal and colonic ischemic events). Symptoms of gastrointestinal and colonic ischemic events include:

- sudden or severe stomach pain
- stomach pain after meals
- weight loss
- fever

- nausea or vomiting
- constipation or diarrhea
- bloody diarrhea

- problems with blood circulation to your legs and feet (peripheral vascular ischemia). Symptoms of peripheral vascular ischemia include:
  - cramping and pain in your legs or hips
  - feeling of heaviness or tightness in your leg muscles
  - burning or aching pain in your feet or toes while resting
  - numbness, tingling, or weakness in your legs
  - cold feeling or color changes in 1 or both legs or feet
- medication overuse headaches. Some people who use too many Sumatriptan nasal sprays may have worse headaches (medication overuse headache). If your headaches get worse, your healthcare provider may decide to stop your treatment with Sumatriptan Nasal Spray.
- serotonin syndrome. Serotonin syndrome is a rare but serious problem that can happen in people using Sumatriptan Nasal Spray, especially if Sumatriptan Nasal Spray is used with anti-depressant medicines called SSRIs or SNRIs.
Call your healthcare provider right away if you have any of the following symptoms of serotonin syndrome:
  1. mental changes such as seeing things that are not there (hallucinations), agitation, or coma
  2. fast heartbeat
  3. changes in blood pressure
  4. high body temperature
  5. tight muscles
  6. trouble walking
- local irritation. Some people who use Sumatriptan Nasal Spray may have irritation of their throat and nose. Symptoms of local irritation of the throat and nose include: burning, numbness, tingling sensation, nasal discharge, pain or soreness.
- hives (itchy bumps); swelling of your tongue, mouth, or throat.
- seizures. Seizures have happened in people taking Sumatriptan Nasal Spray who have never had seizures before. Talk with your healthcare provider about your chance of having seizures while you take Sumatriptan Nasal Spray.

The most common side effects of Sumatriptan Nasal Spray include:

- unusual or bad taste in your mouth
- nausea
- vomiting
- dizziness
- warm, hot, burning feeling

Tell your healthcare provider if you have any side effect that bothers you or that does not go away.

These are not all the possible side effects of Sumatriptan Nasal Spray.

Call your doctor for medical advice about side effects. You may report side effects to FDA at 1-800-FDA-1088.

How should I store Sumatriptan Nasal Spray?

- Store Sumatriptan Nasal Spray between 36°F to 86°F (2°C to 30°C).
- Store your medicine away from light.

Keep Sumatriptan Nasal Spray and all medicines out of the reach of children.

General information about the safe and effective use of Sumatriptan Nasal Spray.

Medicines are sometimes prescribed for purposes other than those listed in Patient Information leaflets. Do not use Sumatriptan Nasal Spray for a condition for which it was not prescribed. Do not give Sumatriptan Nasal Spray to other people, even if they have the same symptoms you have. It may harm them.

This Patient Information leaflet summarizes the most important information about Sumatriptan Nasal Spray. If you would like more information, talk with your healthcare provider. You can ask your healthcare provider or pharmacist for information about Sumatriptan Nasal Spray that is written for healthcare professionals.

What are the ingredients in Sumatriptan Nasal Spray?

Active ingredient: sumatriptan

Inactive ingredients: monobasic potassium phosphate NF, anhydrous dibasic sodium phosphate USP, sulfuric acid NF, sodium hydroxide NF, and purified water USP.

Brands listed are trademarks of their respective owners.
Manufactured by:

GlaxoSmithKline

Durham, NC 27701

Manufactured for:

Prasco Laboratories

Mason, OH 45040 USA

SNS-PS:2PPI

This Patient Information has been approved by the U.S. Food and Drug Administration. Revised March 2024

Instructions for Use

Sumatriptan Nasal Spray

(soo”ma trip’tan)

For use in the nose only. Do not spray in your eyes.

Step 1. Remove the Sumatriptan Nasal Spray unit from the plastic pack (see Figure A).
Do not remove the unit until you are ready to use. The unit contains only 1 spray. Do not test before use.

Figure A

Step 2. While sitting down, gently blow your nose to clear your nasal passages (see Figure B).

Figure B

Step 3. Keeping your head in an upright position, gently close 1 nostril with your index finger and breathe out gently through your mouth (see Figure C).

Figure C

Figure D

Step 4. With your other hand, hold the container with your thumb supporting the container at the bottom, and your index and middle fingers on either side of the nozzle (see Figure D).
Insert the nozzle into your open nostril about ½ inch. Do not press the blue plunger yet.

Figure E

Step 5. Keep your head upright and close your mouth. While gently taking a breath in through your nose, press the blue plunger firmly to release the dose of Sumatriptan Nasal Spray (see Figure E).

Figure F

Step 6. Keep your head level and remove the nozzle from your nostril. While holding your head level, gently breathe in through your nose and out through your mouth for 10 to 20 seconds (see Figure F).
Do not breathe in deeply.

This Patient Information and Instructions for Use have been approved by the U.S. Food and Drug Administration.
Manufactured by:

GlaxoSmithKline

Durham, NC 27701

Manufactured for:

Prasco Laboratories

Mason, OH 45040 USA

March 2024

SNS-PS:2PIL

PACKAGE LABEL

Principal Display Panel

NDC 66993-081-69

Sumatriptan

Nasal Spray

PRASCO

0.1 mL per unit

For Intranasal Use Only

Each unit dose nasal spray contains 5 mg of sumatriptan.

1 Spray per unit.

Do not test before use.

Rx Only

6 Nasal Spray Units

5 mg

Made in India

Rev. 11/19

62000000045655

PACKAGE LABEL

Principal Display Panel

NDC 66993-082-69

Sumatriptan

Nasal Spray

PRASCO

0.1 mL per unit

For Intranasal Use Only

Each unit dose nasal spray contains 20 mg of sumatriptan.

1 Spray per unit.

Do not test before use.

Rx Only

6 Nasal Spray Units

20 mg

Made in India

Rev. 11/19

62000000045654